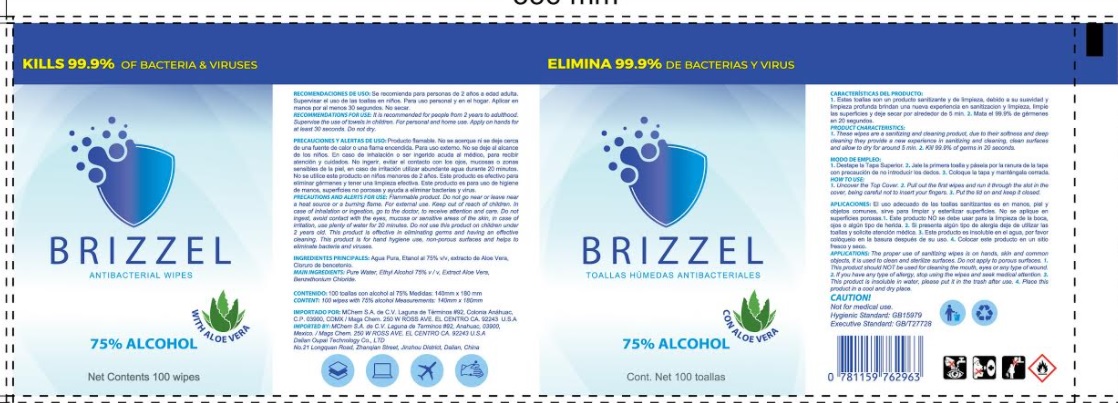 DRUG LABEL: BRIZZEL
NDC: 80303-001 | Form: CLOTH
Manufacturer: MAGS CHEM CORP
Category: otc | Type: HUMAN OTC DRUG LABEL
Date: 20201013

ACTIVE INGREDIENTS: ALCOHOL 75 mL/100 mL
INACTIVE INGREDIENTS: WATER; ALOE VERA LEAF; BENZETHONIUM CHLORIDE

BRIZZEL

Active Ingredient

ALCOHOL 75%

Purpose

ANTIBACTERIAL

Warnings

MAY BE FLAMABLE

KEEP OUT OF REACH OF CHILDREN

DO NOT INGEST

IN CASE OF IRRITATION USE WATER, GET MEDICAL HELP

Uses

ANTIBACTERIAL.

Directions

FOR PERSONAL AND HOME USE, APPLY ON HANDS

Inactive Ingredients

WATER,ALOE VERA,BENZETHONIUM CHLORIDE.